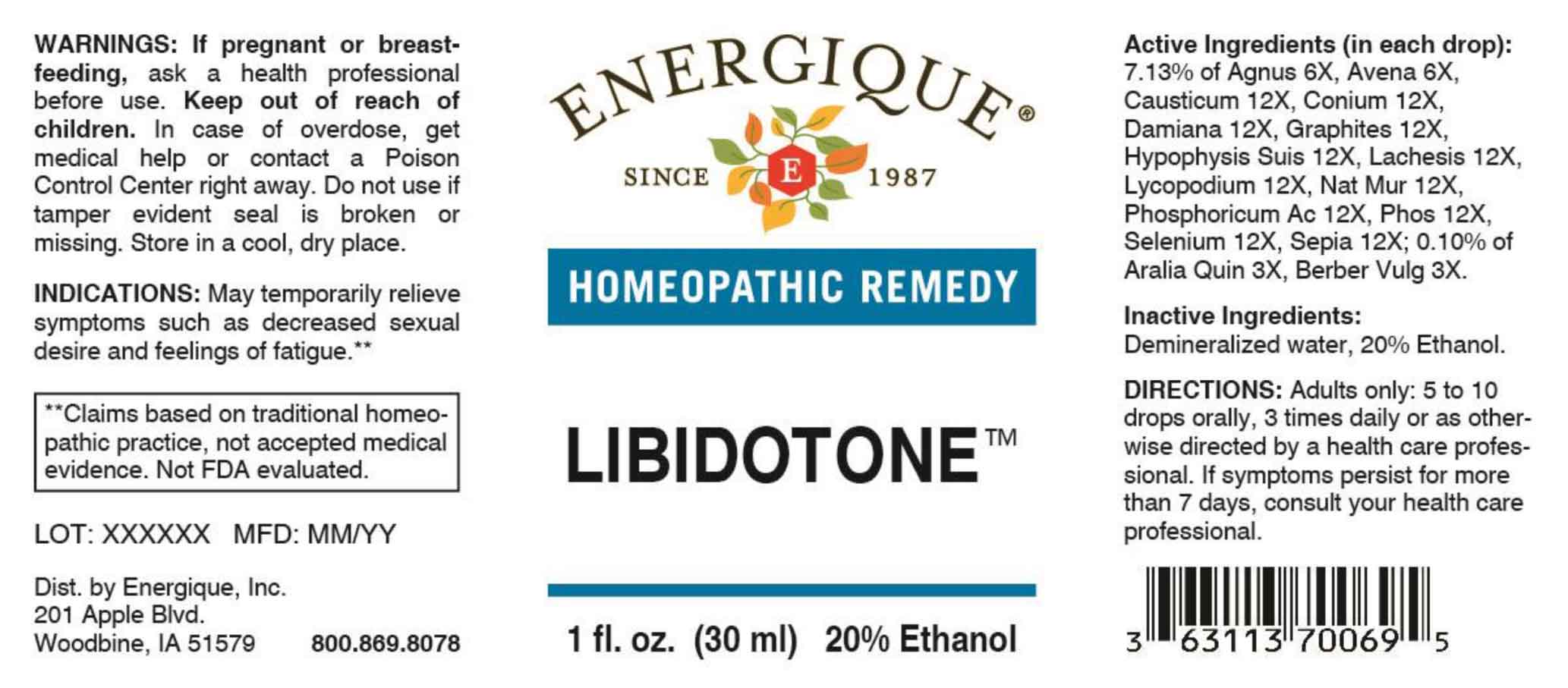 DRUG LABEL: Libidotone
NDC: 44911-0741 | Form: LIQUID
Manufacturer: Energique, Inc.
Category: homeopathic | Type: HUMAN OTC DRUG LABEL
Date: 20260227

ACTIVE INGREDIENTS: AMERICAN GINSENG 3 [hp_X]/1 mL; BERBERIS VULGARIS ROOT BARK 3 [hp_X]/1 mL; CHASTE TREE FRUIT 6 [hp_X]/1 mL; AVENA SATIVA FLOWERING TOP 6 [hp_X]/1 mL; CAUSTICUM 12 [hp_X]/1 mL; CONIUM MACULATUM FLOWERING TOP 12 [hp_X]/1 mL; TURNERA DIFFUSA LEAFY TWIG 12 [hp_X]/1 mL; GRAPHITE 12 [hp_X]/1 mL; SUS SCROFA PITUITARY GLAND 12 [hp_X]/1 mL; LACHESIS MUTA VENOM 12 [hp_X]/1 mL; LYCOPODIUM CLAVATUM SPORE 12 [hp_X]/1 mL; SODIUM CHLORIDE 12 [hp_X]/1 mL; PHOSPHORIC ACID 12 [hp_X]/1 mL; PHOSPHORUS 12 [hp_X]/1 mL; SELENIUM 12 [hp_X]/1 mL; SEPIA OFFICINALIS JUICE 12 [hp_X]/1 mL
INACTIVE INGREDIENTS: WATER; ALCOHOL

DRUG FACTS:

ACTIVE INGREDIENTS:

(in each drop): 7.13% of Agnus Castus 6X, Avena Sativa 6X, Causticum 12X, Conium Maculatum 12X, Damiana 12X, Graphites 12X, Hypophysis Suis 12X, Lachesis Mutus 12X, Lycopodium Clavatum 12X, Natrum Muriaticum 12X, Phosphoricum Acidum 12X, Phosphorus 12X, Selenium Metallicum 12X, Sepia 12X; 0.10% Aralia Quinquefolia 3X, Berberis Vulgaris 3X.

PURPOSE:

May temporarily relieve symptoms such as decreased sexual desire and feelings of fatigue.**

**Claims based on traditional homeopathic practice, not accepted medical evidence, Not FDA evaluated.

WARNINGS:

If pregnant or breast-feeding, ask a health professional before use.

Keep out of reach of children. In case of overdose, get medical help or contact a Poison Control Center right away.

Do not use if tamper evident seal is broken or missing. Store in a cool, dry place.

KEEP OUT OF REACH OF CHILDREN:

In case of overdose, get medical help or contact a Poison Control Center right away.

DIRECTIONS:

Adults only: 5 to 10 drops orally, 3 times daily or as otherwise directed by a health care professional.

If symptoms persist for more than 7 days, consult your health care professional.

USES:

May temporarily relieve symptoms such as decreased sexual desire and feelings of fatigue.**

**Claims based on traditional homeopathic practice, not accepted medical evidence, Not FDA evaluated.

INACTIVE INGREDIENTS:

Demineralized water, 20% Ethanol.

QUESTIONS:

Dist. by Energique, Inc.

201 Apple Blvd.

Woodbine, IA 51579

800.869.8078

PACKAGE LABEL DISPLAY:

ENERGIQUE

SINCE 1987

HOMEOPATHIC REMEDY

LIBIDOTONE

1 fl. oz. (30 ml)